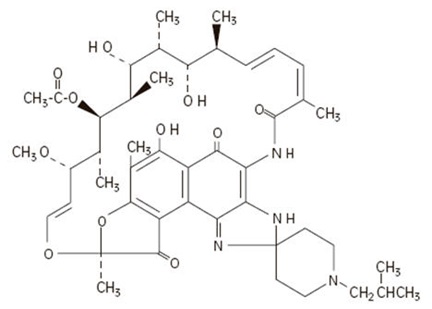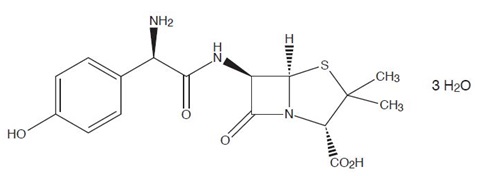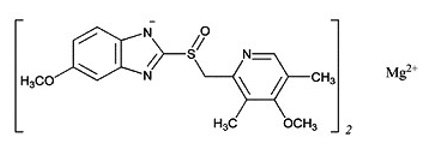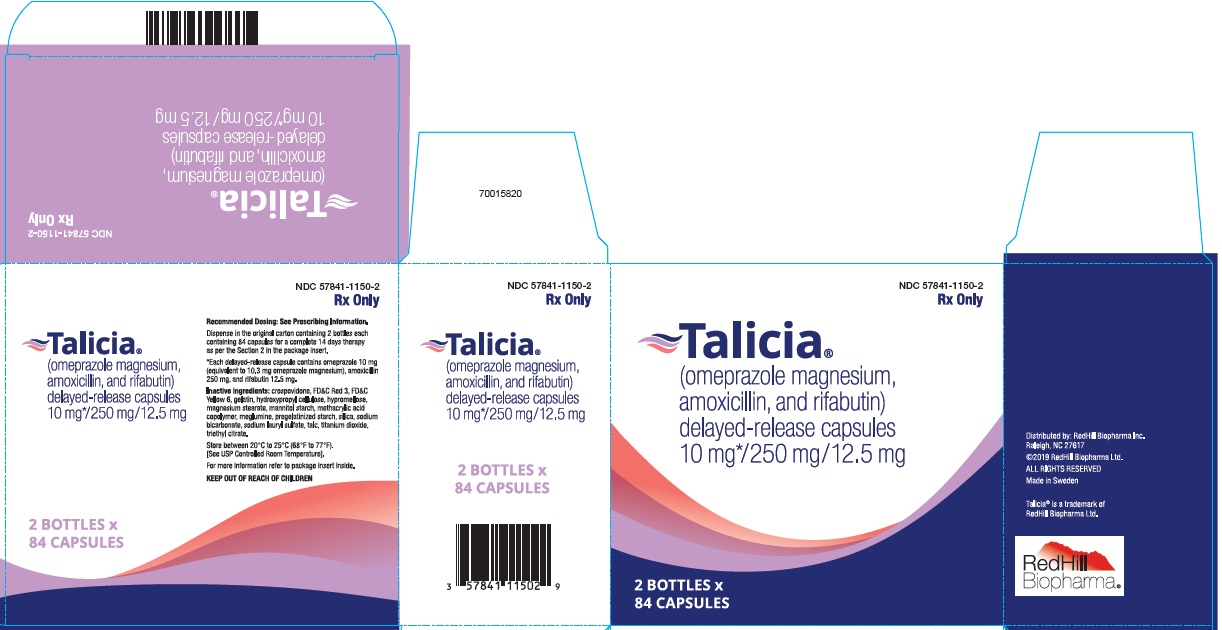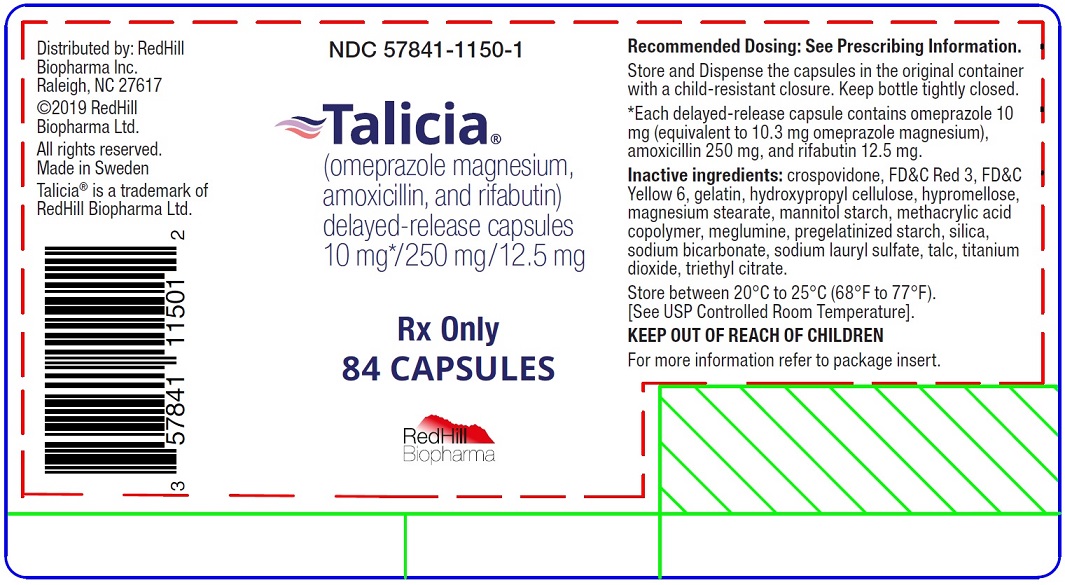 DRUG LABEL: Talicia
NDC: 57841-1150 | Form: CAPSULE, DELAYED RELEASE
Manufacturer: RedHill Biopharma Ltd
Category: prescription | Type: HUMAN PRESCRIPTION DRUG LABEL
Date: 20251223

ACTIVE INGREDIENTS: OMEPRAZOLE MAGNESIUM 10 mg/1 1; AMOXICILLIN 250 mg/1 1; RIFABUTIN 12.5 mg/1 1
INACTIVE INGREDIENTS: CROSPOVIDONE (15 MPA.S AT 5%); FD&C RED NO. 3; FD&C YELLOW NO. 6; GELATIN; HYDROXYPROPYL CELLULOSE, UNSPECIFIED; HYPROMELLOSES; MAGNESIUM STEARATE; MANNITOL; METHACRYLIC ACID - ETHYL ACRYLATE COPOLYMER (1:1) TYPE A; MEGLUMINE; STARCH, CORN; SILICON DIOXIDE; SODIUM BICARBONATE; SODIUM LAURYL SULFATE; TALC; TITANIUM DIOXIDE; TRIETHYL CITRATE

HIGHLIGHTS OF PRESCRIBING INFORMATION

These highlights do not include all the information needed to use TALICIA® safely and effectively. See full prescribing information for TALICIA.
TALICIA (omeprazole magnesium, amoxicillin and rifabutin) delayed-release capsules, for oral use
Initial U.S. Approval: 2019

RECENT MAJOR CHANGES

Dosage and Administration (2) 9/2023

Warnings and Precautions, Drug-Induced Enterocolitis Syndrome (DIES) (5.3) 5/2024

1 INDICATIONS AND USAGE

TALICIA is a three-drug combination of omeprazole, a proton pump inhibitor, amoxicillin, a penicillin-class antibacterial, and rifabutin, a rifamycin antibacterial, indicated for the treatment of Helicobacter pylori infection in adults. (1)

To reduce the development of drug-resistant bacteria and maintain the effectiveness of TALICIA and other antibacterial drugs, TALICIA should be used only to treat or prevent infections that are proven or strongly suspected to be caused by bacteria. (1.2)

2 DOSAGE AND ADMINISTRATION

- Administer four (4) TALICIA capsules three times daily (at least 4 hours apart, e.g., morning, mid-day, and evening) with food for 14 days. (2.1)
- Swallow whole. Do not crush or chew. (2.1)
- Do not take TALICIA with alcohol. (2.1)

3 DOSAGE FORMS AND STRENGTHS

Delayed Release Capsule: Omeprazole 10 mg, (equivalent to 10.3 mg of omeprazole magnesium) amoxicillin 250 mg and rifabutin 12.5 mg. (3)

4 CONTRAINDICATIONS

- Known hypersensitivity to omeprazole, amoxicillin or any other beta-lactam antibacterial drugs, rifabutin or any other rifamycin, or any component of TALICIA. (4.1)
- Rilpivirine-containing products. (4.2)
- Delavirdine. (4.3)
- Voriconazole. (4.4)

5 WARNINGS AND PRECAUTIONS

- Hypersensitivity Reactions: Serious and occasionally fatal reactions (e.g., anaphylaxis) have been reported with components of TALICIA. If hypersensitivity reactions occur, discontinue TALICIA and institute immediate therapy (e.g., anaphylaxis management). (5.1)
- Severe Cutaneous Adverse Reactions (SCAR): There have been reports of SCAR with the components of TALICIA. Monitor closely and discontinue TALICIA at the first signs of SCAR. (5.2)
- Drug-induced enterocolitis syndrome (DIES) has been reported with use of amoxicillin, a component of TALICIA. If this occurs, discontinue TALICIA and institute appropriate therapy. (5.3)
- Clostridioides difficile-Associated Diarrhea (CDAD): Evaluate if diarrhea occurs. (5.4)
- Reduction in the Efficacy of Hormonal Contraceptives: Additional non-hormonal highly effective methods of contraception should be used while taking TALICIA. (5.5)
- Acute Tubulointerstitial Nephritis (TIN): Observed in patients taking Proton Pump Inhibitors (PPIs), including omeprazole and penicillins. Discontinue TALICIA and evaluate patients. (5.6)
- Cutaneous and Systemic Lupus Erythematosus: Mostly cutaneous; new onset or exacerbation of existing disease; discontinue TALICIA and evaluate. (5.8)

6 ADVERSE REACTIONS

Most common adverse reactions (≥1%) were diarrhea, headache, nausea, abdominal pain, chromaturia, rash, dyspepsia, oropharyngeal pain, vomiting, and vulvovaginal candidiasis. (6.1)

To report SUSPECTED ADVERSE REACTIONS, contact RedHill Biopharma Inc. at 1-833-ADRHILL (1-833-237-4455) or FDA at 1-800-FDA-1088 or www.fda.gov/medwatch.

7 DRUG INTERACTIONS

Components of TALICIA have the potential for clinically important drug interactions. See Full Prescribing Information for important drug interactions with TALICIA. (4, 5.7)

8 USE IN SPECIFIC POPULATIONS

- TALICIA may cause fetal harm. (8.1)
- Renal Impairment: Avoid use in severe renal impairment. (8.6)
- Hepatic Impairment: Avoid use. (8.7)

FULL PRESCRIBING INFORMATION

1 INDICATIONS AND USAGE

1.1 Helicobacter pylori Infection

TALICIA is indicated for the treatment of Helicobacter pylori infection in adults [see Clinical Studies (14)].

1.2 Usage

To reduce the development of drug-resistant bacteria and maintain the effectiveness of TALICIA and other antibacterial drugs, TALICIA should be used only to treat or prevent infections that are proven or strongly suspected to be caused by susceptible bacteria. When culture and susceptibility information are available, they should be considered in selecting or modifying antibacterial therapy. In the absence of such data, local epidemiology and susceptibility patterns may contribute to the empiric selection of therapy.

2 DOSAGE AND ADMINISTRATION

2.1 Recommended Dosage

Administer four (4) TALICIA capsules three times daily (at least 4 hours apart, e.g., morning, mid-day, and evening) with food for 14 days. Instruct patients to swallow the TALICIA capsules whole, with a full glass of water (8 ounces). Each dose (4 capsules) of TALICIA includes rifabutin 50 mg, amoxicillin 1,000 mg and omeprazole 40 mg. Do not crush or chew TALICIA capsules. Do not take TALICIA with alcohol.

2.2 Missed Doses

- If a dose is missed and the next dose is not within 4 hours, administer the missed dose as soon as possible.
- If a dose is missed and the next dose is within 4 hours, administer the missed dose as soon as possible and delay the next dose to ensure there are at least 4 hours between two doses.

3 DOSAGE FORMS AND STRENGTHS

Each TALICIA delayed-release capsule contains omeprazole 10 mg (equivalent to 10.3 mg of omeprazole magnesium), amoxicillin 250 mg and rifabutin 12.5 mg. The capsules are orange, opaque, with “RHB” imprinted in black on the capsule cap and “105” imprinted in black on the capsule base.

4 CONTRAINDICATIONS

4.1 Hypersensitivity Reactions

TALICIA is contraindicated in patients with known hypersensitivity to the components of TALICIA: amoxicillin [or other β-lactam antibacterial drugs (e.g., penicillins and cephalosporins)], omeprazole (or other benzimidazoles [e.g. proton pump inhibitors (PPIs) and anthelmintics]), rifabutin (or any other rifamycins), or to any other component of TALICIA. Hypersensitivity reactions may include anaphylaxis or Stevens Johnson Syndrome, anaphylactic shock, angioedema, bronchospasm, acute tubulointerstitial nephritis, rash and urticaria [see Warnings and Precautions (5.1, 5.6, 5.8), Adverse Reactions (6.1)].

4.2 Rilpivirine-containing Products

Proton pump inhibitors (PPIs), including omeprazole (a component of TALICIA), are contraindicated in patients receiving rilpivirine-containing products [see Drug Interactions (7.1)].

4.3 Delavirdine

The use of rifabutin (a component of TALICIA), is contraindicated in patients receiving delavirdine [see Drug Interactions (7.1)].

4.4 Voriconazole

The use of rifabutin (a component of TALICIA), is contraindicated in patients receiving voriconazole [see Drug Interactions (7.1)].

5 WARNINGS AND PRECAUTIONS

5.1 Hypersensitivity Reactions

Serious and fatal hypersensitivity reactions, e.g., anaphylaxis, angioedema, erythema multiforme, exfoliative dermatitis, hypersensitivity vasculitis, acute tubulointerstitial nephritis, and serum sickness have been reported with the components of TALICIA: omeprazole, amoxicillin and rifabutin.

Signs and symptoms of these reactions may include hypotension, urticaria, angioedema, acute bronchospasm, conjunctivitis, thrombocytopenia, neutropenia or flu-like syndrome (weakness, fatigue, muscle pain, nausea, vomiting, headache, fever, chills, aches, rash, itching, sweats, dizziness, shortness of breath, chest pain, cough, syncope, palpitations).

There have been reports of individuals with a history of penicillin hypersensitivity who have experienced severe reactions when treated with cephalosporins.

Before initiating therapy with TALICIA, inquire about history of hypersensitivity reactions to penicillins, cephalosporins, rifamycins, or PPIs. Discontinue TALICIA and institute immediate therapy, if hypersensitivity reactions occur.

5.2 Severe Cutaneous Adverse Reactions

Severe cutaneous adverse reactions (SCAR), such as Stevens-Johnson syndrome (SJS), toxic epidermal necrolysis (TEN), drug reaction with eosinophilia and systemic symptoms (DRESS), and acute generalized exanthematous pustulosis (AGEP) have been reported with the components of TALICIA: rifabutin, amoxicillin, and omeprazole [see Warnings and Precautions (5.1) and Adverse Reactions (6.3)].

Monitor closely and discontinue TALICIA at the first signs of SCAR.

5.3 Drug-Induced Enterocolitis Syndrome (DIES)

Drug-induced enterocolitis syndrome (DIES) has been reported with use of amoxicillin, a component of TALICIA [see Adverse Reactions (6.3)], with most cases occurring in pediatric patients ≤18 years of age. DIES is a non-IgE mediated hypersensitivity reaction characterized by protracted vomiting occurring 1 to 4 hours after drug ingestion in the absence of skin or respiratory symptoms. DIES may be associated with pallor, lethargy, hypotension, shock, diarrhea within 24 hours after ingesting amoxicillin, and leukocytosis with neutrophilia. If DIES occurs, discontinue TALICIA and institute appropriate therapy.

5.4 Clostridioides difficile-Associated Diarrhea

Clostridioides difficile-associated diarrhea (CDAD) has been reported with use of omeprazole, a component of TALICIA and nearly all antibacterial agents, including amoxicillin and rifabutin, which are components of TALICIA and may range in severity from mild diarrhea to fatal colitis. Treatment with antibacterial agents alters the normal flora of the colon leading to overgrowth of C. difficile.

CDAD must be considered in all patients who present with diarrhea following proton pump inhibitor and or antibacterial use. Careful medical history is necessary since CDAD has been reported to occur over two months after the administration of antibacterial agents.

If CDAD is confirmed, TALICIA should be discontinued. Appropriate fluid and electrolyte management, protein supplementation, antibacterial drug treatment of C. difficile, and surgical evaluation should be instituted as clinically indicated.

5.5 Reduced Efficacy of Hormonal Contraceptives

TALICIA may reduce the efficacy of hormonal contraceptives. Therefore, an additional non-hormonal highly effective method of contraception should be used while taking TALICIA [see Drug Interactions (7.1)].

5.6 Acute Tubulointerstitial Nephritis

Acute tubulointerstitial nephritis (TIN) has been observed in patients taking PPIs including omeprazole, a component of TALICIA. TIN may occur at any point during PPI therapy.

Patients may present with varying signs and symptoms from symptomatic hypersensitivity reactions, to non-specific symptoms of decreased renal function (e.g., malaise, nausea, anorexia). In reported case series, some patients were diagnosed on biopsy and in the absence of extra-renal manifestations (e.g., fever, rash or arthralgia).

TIN has also been observed in patients taking penicillins, such as amoxicillin, a component of TALICIA.

Discontinue TALICIA and evaluate patients with suspected acute TIN [see Contraindications (4)].

5.7 Risk of Adverse Reactions or Loss of Efficacy Due to Drug Interactions

Components of TALICIA have the potential for clinically important drug interactions [see Contraindications (4) and Drug Interactions (7)].

Avoid concomitant use of TALICIA with other CYP2C19 or CYP3A4 inducers (e.g., St. John’s Wort, rifampin) as they can substantially decrease omeprazole concentrations. Avoid concomitant use of TALICIA with CYP2C19 and/or CYP3A4 inhibitors (e.g., fluconazole, itraconazole) as it may significantly increase the plasma concentration of component (s) of TALICIA. Depending on the protease inhibitor, the concomitant use of TALICIA should be avoided (e.g., amprenavir, indinavir) or dose adjustments for a concomitantly administered protease inhibitor(s) may be required. Concomitant use of PPIs with methotrexate (primarily at high dose) may elevate and prolong serum levels of methotrexate and/or its metabolite, possibly leading to methotrexate toxicities. Avoid TALICIA in patients on high-dose methotrexate. Concomitant use of clopidogrel and omeprazole reduces the pharmacological activity of clopidogrel. Avoid TALICIA in patients on clopidogrel. When using TALICIA, consider alternative anti-platelet therapy [see Drug Interactions (7)].

5.8 Cutaneous and Systemic Lupus Erythematosus

Cutaneous lupus erythematosus (CLE) and systemic lupus erythematosus (SLE) have been reported in patients taking PPIs, including omeprazole. These events have occurred as both new onset and an exacerbation of existing autoimmune disease. The majority of PPI-induced lupus erythematosus cases were CLE. If signs or symptoms consistent with CLE or SLE develop in patients receiving TALICIA, discontinue the drug and evaluate as appropriate.

5.9 Rash in Patients with Mononucleosis

A high percentage of patients with mononucleosis who receive amoxicillin develop an erythematous skin rash. Avoid TALICIA in patients with mononucleosis.

5.10 Uveitis

Due to the possible occurrence of uveitis, patients should be carefully monitored when rifabutin, a component of TALICIA, is given in combination with clarithromycin (or other macrolides) and/or fluconazole and related compounds. If uveitis is suspected, refer for an ophthalmologic evaluation and, if considered necessary, suspend treatment with rifabutin [see Adverse Reactions (6.2)].

5.11 Interactions with Diagnostic Investigations for Neuroendocrine Tumors

Serum chromogranin A (CgA) levels increase secondary to drug-induced decreases in gastric acidity. The increased CgA level may cause false positive results in diagnostic investigations for neuroendocrine tumors. Assess CgA levels at least 14 days after TALICIA treatment and consider repeating the test if initial CgA levels are high [see Drug Interactions (7)].

5.12 Development of Drug-Resistant Bacteria

Prescribing TALICIA either in the absence of a proven or strongly suspected bacterial infection or a prophylactic indication is unlikely to provide benefit to the patient and increases the risk of the development of drug-resistant bacteria.

6 ADVERSE REACTIONS

The following serious adverse reactions are described below and elsewhere in labeling:

- Hypersensitivity Reactions [see Warnings and Precautions (5.1)]
- Severe Cutaneous Adverse Reactions [see Warnings and Precautions (5.2)]
- Drug-Induced Enterocolitis Syndrome (DIES) [see Warnings and Precautions (5.3)]
- Clostridioides difficile-Associated Diarrhea [see Warnings and Precautions (5.4)]
- Acute Tubulointerstitial Nephritis [see Warnings and Precautions (5.6)]
- Cutaneous and Systemic Lupus Erythematosus [see Warnings and Precautions (5.8)]
- Rash in Patients with Mononucleosis [see Warnings and Precautions (5.9)]
- Uveitis [see Warnings and Precautions (5.10)]

6.1 Clinical Trials Experience with TALICIA

Because clinical trials are conducted under widely varying conditions, adverse reaction rates observed in the clinical trials of a drug cannot be directly compared to rates in the clinical trials of another drug and may not reflect the rates observed in practice.

The safety of TALICIA was assessed in adult patients who were screened and found to be positive for H. pylori infection in one active-controlled (Study 1) and one placebo-controlled (Study 2) clinical trial. Patients received TALICIA, amoxicillin and omeprazole, or placebo every eight hours for 14 consecutive days taken with food. A total of 305 patients received TALICIA in Studies 1 and 2, 227 patients received amoxicillin and omeprazole (as omeprazole magnesium) in Study 1, and 41 patients received placebo in Study 2. These patients had a mean age of 46.4 years (range 18 to 70 years); 62.3% were female, 80.3% were white with 64.2% Hispanic or Latino.

Adverse Reactions Leading to Discontinuation

Treatment discontinuation due to an adverse reaction occurred in 1% (4/305) of patients receiving TALICIA, <1% (1/227) of patients receiving amoxicillin and omeprazole, and 2% (1/41) of patients receiving placebo. Adverse reactions leading to discontinuation of TALICIA were nausea and vomiting, nausea, nasal congestion, and nasopharyngitis, in one patient each.

Most Common Adverse Reactions

Selected adverse reactions occurring in ≥1% of patients receiving TALICIA in Study 1 and 2 are described in Table 1.

Table 1: Selected Adverse Reactions Occurring in 1% or Greater of Patients Receiving TALICIA in Studies 1 and 2

 | Study 1 |  | Study 2
Adverse Reaction | TALICIA (N=228) n (%) | Amoxicillin and Omeprazole (N=227) n (%) | TALICIA (N=77) n (%) | Placebo (N=41) n (%)
Diarrhea | 23 (10.1) | 18 (7.9) | 11 (14.3) | 4 (9.8)
Headachea | 17 (7.5) | 16 (7.0) | 12 (15.6) | 4 (9.8)
Nausea | 11 (4.8) | 12 (5.3) | 3 (3.9) | 1 (2.4)
Abdominal painb | 8 (3.5) | 11 (4.8) | 3 (3.9) | 2 (4.9)
Chromaturiac | 0 | 0 | 10 (13.0) | 1 (2.4)
Rashd | 6 (2.6) | 2 (0.9) | 4 (5.2) | 0
Dyspepsiae | 5 (2.2) | 3 (1.3) | 1 (1.3) | 0
Vomiting | 5 (2.2) | 5 (2.2) | 1 (1.3) | 2 (4.9)
Oropharyngeal pain | 2 (0.9) | 2 (0.9) | 3 (3.9) | 0
Vulvovaginal candidiasisf | 5 (2.2) | 5 (2.2) | 0 | 0
a Headache includes: headache and migraine.
b Abdominal pain includes: abdominal pain, abdominal pain upper, and abdominal pain lower.
c Riboflavin was administered in Study 1 to prevent unintentional unblinding and may have contributed to under-reporting of chromaturia.
d Rash includes: rash, rash maculo-papular, rash morbilliform, and urticaria.
e Dyspepsia includes: dyspepsia and epigastric discomfort.
f Vulvovaginal candidiasis includes: vulvovaginal candidiasis, vulvovaginal mycotic infection, fungal infection, and vaginal discharge + vulvovaginal burning sensation + vulvovaginal pruritus.

6.2 Other Important Adverse Reactions from the Labeling of the Individual Components of TALICIA

Additional adverse reactions that occurred in 1% or greater of patients treated with omeprazole or rifabutin alone in clinical trials were as follows:

Omeprazole

Flatulence, acid regurgitation, upper respiratory infection, constipation, dizziness, asthenia, back pain, and cough.

Rifabutin

Flatulence, asthenia, chest pain, fever, pain, leucopenia, anemia, anorexia, eructation, myalgia, insomnia, and taste perversion.

The following selected adverse reactions occurred in less than 1% of patients treated with rifabutin alone: flu-like syndrome, hepatitis, hemolysis, arthralgia, myositis, dyspnea, skin discoloration, thrombocytopenia, pancytopenia, and jaundice.

6.3 Post-Marketing Experience with Components of TALICIA

Because these reactions are voluntarily reported from a population of uncertain size, it is not always possible to reliably estimate their actual frequency or establish a causal relationship to drug exposure.

Omeprazole

Cardiovascular: angina, tachycardia, bradycardia, palpitations, elevated blood pressure, peripheral edema

Endocrine: gynecomastia

Gastrointestinal: pancreatitis including fatal pancreatitis, anorexia, irritable colon, fecal discoloration, mucosal atrophy of the tongue, stomatitis, abdominal swelling, dry mouth, microscopic colitis, fundic gland polyps, gastroduodenal carcinoids in patients with Zollinger-Ellison syndrome on long-term treatment as a manifestation of the underlying condition associated with such tumors

Hepatic: fatal hepatic failure or necrosis, hepatic encephalopathy, hepatocellular disease, cholestatic disease, mixed hepatitis, jaundice

Metabolism and Nutritional disorders: hypoglycemia, hypomagnesemia, with or without hypocalcemia and/or hypokalemia, hyponatremia, weight gain

Musculoskeletal: muscle weakness, myalgia, muscle cramps, joint pain, leg pain, bone fracture.

Nervous System/Psychiatric: depression, agitation, aggression, hallucinations, confusion, insomnia, nervousness, apathy, somnolence, anxiety, dream abnormalities, tremors, paresthesia, vertigo

Respiratory: epistaxis

Skin and subcutaneous tissue disorders: SCAR such as SJS, TEN, DRESS, AGEP, photosensitivity, urticaria, pruritus, petechiae, purpura, alopecia, dry skin, hyperhidrosis

Special Senses: tinnitus, taste perversion

Ocular: optic atrophy, optic neuritis, dry eye syndrome, ocular irritation, blurred vision, double vision

Urogenital: hematuria, proteinuria, elevated serum creatinine, microscopic pyuria, urinary tract infection, glycosuria, urinary frequency, testicular pain, erectile dysfunction

Hematologic: Agranulocytosis, hemolytic anemia, pancytopenia, neutropenia, anemia, thrombocytopenia, leukopenia, leukocytosis

Amoxicillin

Gastrointestinal: Drug-induced enterocolitis syndrome (DIES), black hairy tongue

Liver: hepatic dysfunction, cholestatic jaundice, cholestasis, acute cytolytic hepatitis

Renal: crystalluria [see Overdosage (10)]

Hemic and Lymphatic Systems: anemia, hemolytic anemia, thrombocytopenia, thrombocytopenic purpura, eosinophilia, leukopenia, and agranulocytosis

Central Nervous System: hyperactivity, agitation, anxiety, insomnia, confusion, convulsions, aseptic meningitis, behavioral changes, and/or dizziness

Skin and subcutaneous tissue disorders: SCAR, such as SJS, TEN, DRESS, and AGEP, and linear IgA bullous dermatosis.

Rifabutin

Blood and lymphatic system disorders: agranulocytosis, lymphopenia

Skin and subcutaneous tissue disorders: SCAR, such as SJS, TEN, DRESS, and AGEP.

7 DRUG INTERACTIONS

7.1 Interactions with Other Drugs and Diagnostics

Drug interaction studies with TALICIA have not been conducted. The drug interaction information described here is based on the prescribing information of individual TALICIA components: omeprazole, amoxicillin, and rifabutin.

Rifabutin is a substrate and inducer of cytochrome P450 (CYP) 3A enzymes. Omeprazole is a substrate and an inhibitor of CYP2C19, and a substrate of CYP3A4. Co-administration of TALICIA and other drugs that are substrates, inhibitors, or inducers of these enzymes may alter concentrations of rifabutin/omeprazole or other co-administered drugs [See Table 2 below and Clinical Pharmacology (12.3)].

Omeprazole magnesium is a PPI. Refer to the prescribing information of the drugs used concomitantly with TALICIA for further information on their interactions with PPIs.

Table 2: Interactions with TALICIA When Co-Administered with Other Drugs and Diagnostics

CYP2C19 or CYP3A4 Inducers
Clinical Impact | Decreased exposure of omeprazole when used concomitantly with strong inducers.
Prevention or Management | St. John’s Wort, rifampin: Avoid concomitant use with TALICIA [see Warnings and Precautions (5.7)].; Ritonavir-containing products: See prescribing information for specific drugs.
CYP2C19 or CYP3A4 Inhibitors
Clinical Impact | Increased blood levels of omeprazole and rifabutin.
Prevention or Management | Voriconazole: Concomitant use with TALICIA is contraindicated [see Contraindications (4)].; Fluconazole, posaconazole and itraconazole: Avoid concomitant use with TALICIA. If coadministration cannot be avoided, monitor patients for rifabutin associated adverse events, and lack of anti-fungal efficacy.
CYP2C19 Substrates (e.g., Clopidogrel, citalopram, cilostazol, phenytoin, diazepam)
Clinical Impact | Increased plasma concentrations of CYP2C19 substrate drugs or decreased/increased plasma concentrations of its active metabolite(s) [see Clinical Pharmacology (12.3)].
Prevention or Management | Clopidogrel: Consider use of alternative anti-platelet therapy [see Warnings and Precautions (5.7)]. Avoid concomitant use with TALICIA.
Antiretrovirals/Protease Inhibitors
Clinical Impact | Antiretrovirals/protease inhibitors may increase rifabutin blood levels.; The effect of PPIs (such as omeprazole in TALICIA) on antiretroviral drugs is variable. The clinical importance and the mechanisms behind these interactions are not always known.; - Decreased exposure of some antiretroviral drugs (e.g., rilpivirine, atazanavir, and nelfinavir) when used concomitantly with omeprazole may reduce antiviral effect and promote the development of drug resistance [see Clinical Pharmacology (12.3)]. - Increased exposure of other antiretroviral drugs (e.g., saquinavir) when used concomitantly with omeprazole may increase toxicity [see Clinical Pharmacology (12.3)].; There are other antiretroviral drugs which do not result in clinically relevant interactions with omeprazole.
Prevention or Management | Delavirdine: Combination treatment with TALICIA and delavirdine is contraindicated [see Contraindications (4)].; Rilpivirine-containing products: Concomitant use with TALICIA is contraindicated [see Contraindications (4)].; Avoid concomitant use of TALICIA with amprenavir, indinavir, lopinavir/ritonavir, saquinavir/ritonavir, ritonavir, tipranavir/ritonavir, fosamprenavir/ritonavir, or nelfinavir [see Warnings and Precautions (5.7)].; Other antiretrovirals: See prescribing information for specific antiretroviral drugs.
Probenecid
Clinical Impact | Increased and prolonged blood levels of amoxicillin.
Allopurinol
Clinical Impact | Increase in the incidence of rashes is reported in patients receiving both allopurinol and amoxicillin together compared to patients receiving amoxicillin alone. It is not known whether this potentiation of amoxicillin rashes is due to allopurinol or the hyperuricemia present in these patients.
Prevention or Management | Discontinue allopurinol at the first appearance of skin rash. Assess benefit-risk of continuing TALICIA treatment.
Warfarin, and Other Oral Anticoagulants
Clinical Impact | Abnormal prolongation of prothrombin time (increased international normalized ratio [INR]) has been reported in patients receiving amoxicillin and oral anticoagulants and in patients receiving PPIs, including omeprazole, and warfarin concomitantly.; Increases in INR and prothrombin time may lead to abnormal bleeding and even death.
Prevention or Management | Monitor INR and prothrombin time and adjust the dose of warfarin or other oral anticoagulants to maintain the desired level of anticoagulation.
Methotrexate
Clinical Impact | Concomitant use of omeprazole with methotrexate (primarily at high doses) may elevate and prolong serum levels of methotrexate and/or its metabolite hydroxymethotrexate, possibly leading to methotrexate toxicities [see Warnings and Precautions (5.7)].
Prevention or Management | Avoid concomitant use of TALICIA in patients receiving high-dose methotrexate.
Digoxin
Clinical Impact | Potential for increased digoxin blood levels [see Clinical Pharmacology (12.3)].
Prevention or Management | Monitor digoxin concentrations. Dose adjustment may be needed to maintain therapeutic drug concentrations. See digoxin prescribing information.
Drugs Dependent on Gastric pH for Absorption (e.g., iron salts, erlotinib, dasatinib, nilotinib, mycophenolate mofetil, ketoconazole/itraconazole)
Clinical Impact | Omeprazole can alter the absorption of other drugs due to its effect of reducing intragastric acidity thereby increasing gastric pH.
Prevention or Management | Mycophenolate mofetil (MMF): Use TALICIA with caution in transplant patients receiving MMF [see Clinical Pharmacology (12.3)].; See the prescribing information of other drugs dependent on gastric pH for absorption.
Tacrolimus
Clinical Impact | Potential for increased tacrolimus blood levels, especially in patients who are intermediate or poor metabolizers of CYP2C19.
Prevention or Management | Monitor tacrolimus whole blood levels and adjust dose as per the prescribing information for tacrolimus.
Drugs Metabolized via the CYP450 Enzymes (e.g., cyclosporine, disulfiram)
Clinical Impact | Interactions are reported with omeprazole and other drugs metabolized via the CYP450 enzymes.
Prevention or Management | Monitor patients to determine if it is necessary to adjust the dosage of these other drugs when taken concomitantly with TALICIA.
Oral Contraceptives
Clinical Impact | Concomitant use of amoxicillin and rifabutin with hormonal contraceptives may lead to loss of its efficacy due to lower estrogen reabsorption and decreased ethinylestradiol and norethindrone concentrations, respectively [see Warnings and Precautions (5.5)].
Prevention or Management | Patients should be advised to use additional or alternative non-hormonal methods of contraception.
Diagnostic Investigations for Neuroendocrine Tumors
Clinical Impact | PPI-induced decrease in gastric acidity may lead to increased serum chromogranin A (CgA) levels, which may cause false positive results in diagnostics for neuroendocrine tumors [see Warnings and Precautions (5.11)].
Prevention or Management | Assess CgA levels at least 14 days after stopping TALICIA treatment and consider repeating the test if initial CgA levels are high. If serial tests are performed (e.g., for monitoring), the same commercial laboratory should be used for testing, as reference ranges between tests may vary.
Urine Glucose Test
Clinical Impact | High urine concentrations of ampicillin or amoxicillin may result in false-positive reactions when using glucose tests based on the Benedict’s copper reduction reaction that determines the amount of reducing substances like glucose in the urine.
Prevention or Management | Glucose tests based on enzymatic glucose oxidase reactions should be used.
Interaction with Secretin Stimulation Test
Clinical Impact | Hyper-response in gastrin secretion in response to secretin stimulation test may falsely suggest gastrinoma.
Prevention or Management | Test should be performed at least 14 days after stopping TALICIA treatment to allow gastrin levels to return to baseline.
False Positive Urine Tests for Tetrahydrocannabinol (THC)
Clinical Impact | There have been reports of false positive urine screening tests for THC in patients receiving PPIs.
Prevention or Management | An alternative confirmatory method should be considered to verify positive results.
Other Laboratory Tests
Clinical Impact | Following administration of ampicillin or amoxicillin to pregnant women, a transient decrease in plasma concentration of total conjugated estriol, estriol-glucuronide, conjugated estrone, and estradiol has been noted.

8 USE IN SPECIFIC POPULATIONS

8.1 Pregnancy

Risk Summary

Based on animal reproduction studies, TALICIA may cause fetal harm when administered to pregnant women. There are no adequate and well controlled studies of amoxicillin, omeprazole, or rifabutin (used separately or together) in pregnant women. Use of TALICIA is generally not recommended for use in pregnancy. If TALICIA is used during pregnancy, advise pregnant women of the potential risk to a fetus.

Omeprazole: Available epidemiologic data do not demonstrate an increased risk of major congenital malformations or other adverse pregnancy outcomes with first trimester omeprazole use. Reproduction studies in rats and rabbits resulted in dose-dependent embryo-lethality at omeprazole doses that were approximately 1.13 to 11 times an oral human dose of 120 mg.

Fetal malformations were not observed in animal reproduction studies with administration of oral esomeprazole (an enantiomer of omeprazole) magnesium in rats and rabbits during organogenesis with doses about 23 times and 14 times, respectively, of an oral human dose of 120 mg esomeprazole or omeprazole. Changes in bone morphology were observed in offspring of rats dosed through most of pregnancy and lactation at doses equal to or greater than approximately 11 times an oral human dose of 120 mg esomeprazole or omeprazole. When maternal administration was confined to gestation only, there were no effects on bone physeal morphology in the offspring at any age [see Data].

Amoxicillin: Available data from published epidemiologic studies and pharmacovigilance case reports over several decades with amoxicillin use have not established drug-associated risks of major birth defects, miscarriage, or adverse maternal or fetal outcomes [see Data]. No adverse developmental effects were observed in animal reproduction studies with administration of amoxicillin to pregnant mice and at doses up to 3 to 6 times an oral human dose of 3 grams.

Rifabutin: Fetal malformations were not observed in rat or rabbit reproduction studies given rifabutin at dose levels up to 200 mg/kg (6 to 13 times the recommended human dose). In rats, given rifabutin at 200 mg/kg/day (about 6 times the recommended human daily dose), there was a decrease in fetal viability. Increased skeletal anomalies were observed in rats and rabbits at 40 and 80 mg/kg/day, respectively (corresponding to approximately an equivalent dose and 5 times the recommended human daily dose); maternal toxicity was noted at 80 mg/kg in rabbits [see Data].

The estimated background risks of major birth defects and miscarriage for the indicated population are unknown. All pregnancies have a background risk of birth defect, loss, or other adverse outcomes. In the US general population, the estimated background risk of major birth defects and miscarriage in clinically recognized pregnancies is 2% to 4% and 15% to 20%, respectively.

Data

Human Data

Omeprazole

Four published epidemiological studies compared the frequency of congenital abnormalities among infants born to women who used omeprazole during pregnancy with the frequency of abnormalities among infants of women exposed to H2-receptor antagonists or other controls.

A population-based retrospective cohort epidemiological study from the Swedish Medical Birth Registry, covering approximately 99% of pregnancies, from 1995 to 99, reported on 955 infants (824 exposed during the first trimester with 39 of these exposed beyond first trimester, and 131 exposed after the first trimester) whose mothers used omeprazole during pregnancy. The number of infants exposed in utero to omeprazole that had any malformation, low birth weight, low Apgar score, or hospitalization was similar to the number observed in this population. The number of infants born with ventricular septal defects and the number of stillborn infants was slightly higher in the omeprazole-exposed infants than the expected number in this population.

A population-based retrospective cohort study covering all live births in Denmark from 1996 to 2009, reported on 1,800 live births whose mothers used omeprazole during the first trimester of pregnancy and 837,317 live births whose mothers did not use any proton pump inhibitor. The overall rate of birth defects in infants born to mothers with first trimester exposure to omeprazole was 2.9% and 2.6% in infants born to mothers not exposed to any proton pump inhibitor during the first trimester.

A retrospective cohort study reported on 689 pregnant women exposed to either H2-blockers or omeprazole in the first trimester (134 exposed to omeprazole) and 1,572 pregnant women unexposed to either during the first trimester. The overall malformation rate in offspring born to mothers with first trimester exposure to omeprazole, an H2-blocker, or were unexposed was 3.6%, 5.5%, and 4.1% respectively.

A small prospective observational cohort study followed 113 women exposed to omeprazole during pregnancy (89% with first trimester exposures). The reported rate of major congenital malformations was 4% in the omeprazole group, 2% in controls exposed to non-teratogens, and 2.8% in disease-paired controls. Rates of spontaneous and elective abortions, preterm deliveries, gestational age at delivery, and mean birth weight were similar among the groups.

Several studies have reported no apparent adverse short-term effects on the infant when single dose oral or intravenous omeprazole was administered to over 200 pregnant women as premedication for cesarean section under general anesthesia.

Amoxicillin

While available studies cannot definitively establish the absence of risk, published epidemiological data and post-marketing case reports have not reported a consistent association with amoxicillin and major birth defects, miscarriage, or adverse maternal or fetal outcomes when amoxicillin was used during pregnancy. Available studies have methodologic limitations, including small sample size, retrospective data collection, under-capture of non-live births, exposure misclassification and inconsistent comparator groups.

Rifabutin

Small retrospective observational studies evaluated the use of rifabutin (in combination with other drugs) for treatment of tuberculosis during pregnancy. Available studies were inconclusive in determining whether rifabutin use during pregnancy was associated with adverse effects in the pregnant woman or neonates.

Animal Data

Omeprazole

Reproductive studies conducted with omeprazole in rats at oral doses up to 138 mg/kg/day (about 11 times an oral human dose of 120 mg on a body surface area basis) and in rabbits at doses up to 69.1 mg/kg/day (about 11 times an oral human dose of 120 mg on a body surface area basis) during organogenesis did not show fetal malformations. In rabbits, omeprazole in a dose range of 6.9 to 69.1 mg/kg/day (about 1 to 11 times an oral human dose of 120 mg on a body surface area basis) administered during organogenesis produced dose-related increases in embryo-lethality, fetal resorptions, and pregnancy disruptions. In rats, dose-related embryo/fetal toxicity and postnatal developmental toxicity were observed in offspring resulting from parents treated with omeprazole at 13.8 to 138.0 mg/kg/day (about 1 to 11 times an oral human dose of 120 mg on a body surface area basis), administered prior to mating through the lactation period.

Esomeprazole

The data described below was generated from studies using esomeprazole, an enantiomer of omeprazole. The animal to human dose multiples are based on the assumption of equal systemic exposure to esomeprazole in humans following oral administration of either 120 mg esomeprazole or 120 mg omeprazole.

No effects on embryo-fetal development were observed in reproduction studies with esomeprazole magnesium in rats at oral doses up to 280 mg/kg/day (about 23 times an oral human dose of 120 mg on a body surface area basis) or in rabbits at oral doses up to 86 mg/kg/day (about 14 times an oral human dose of 120 mg esomeprazole or omeprazole on a body surface area basis) administered during organogenesis.

A pre-and postnatal developmental toxicity study in rats with additional endpoints to evaluate bone development was performed with esomeprazole magnesium at oral doses of 14 to 280 mg/kg/day (about 1 to 23 times an oral human dose of 120 mg esomeprazole or omeprazole on a body surface area basis). Neonatal/early postnatal (birth to weaning) survival was decreased at doses equal to or greater than 138 mg/kg/day (about 11 times an oral human dose of 120 mg esomeprazole or omeprazole on a body surface area basis). Body weight and body weight gain were reduced and neurobehavioral or general developmental delays in the immediate post-weaning timeframe were evident at doses equal to or greater than 69 mg/kg/day (about 6 times an oral human dose of 120 mg esomeprazole or omeprazole on a body surface area basis). In addition, decreased femur length, width and thickness of cortical bone, decreased thickness of the tibial growth plate and minimal to mild bone marrow hypocellularity were noted at doses equal to or greater than 14 mg/kg/day (about equivalent to the oral human dose of 120 mg esomeprazole or omeprazole on a body surface area basis). Physeal dysplasia in the femur was observed in offspring of rats treated with oral doses of esomeprazole magnesium at doses equal to or greater than 138 mg/kg/day (about 11 times an oral human dose of 120 mg esomeprazole or omeprazole on a body surface area basis).

Effects on maternal bone were observed in pregnant and lactating rats in the pre-and postnatal toxicity study when esomeprazole magnesium was administered at oral doses of 14 to 280 mg/kg/day (about 1 to 23 times an oral human dose of 120 mg esomeprazole or omeprazole on a body surface area basis). When rats were dosed from gestational day 7 through weaning on postnatal day 21, a statistically significant decrease in maternal femur weight of up to 14% (as compared to placebo treatment) was observed at doses equal to or greater than 138 mg/kg/day (about 11 times an oral human dose of 120 mg esomeprazole or omeprazole on a body surface area basis).

A pre-and postnatal development study in rats with esomeprazole strontium (using equimolar doses compared to esomeprazole magnesium study) produced similar results in dams and pups as described above.

A follow up developmental toxicity study in rats with further time points to evaluate pup bone development from postnatal day 2 to adulthood was performed with esomeprazole magnesium at oral doses of 280 mg/kg/day (about 23 times an oral human dose of 120 mg on a body surface area basis) where esomeprazole administration was from either gestational day 7 or gestational day 16 until parturition. When maternal administration was confined to gestation only, there were no effects on bone physeal morphology in the offspring at any age.

Amoxicillin

Reproduction studies have been performed in mice and rats at doses up to 2000 mg/kg (3 and 6 times the 3 g human dose, based on body surface area). There was no evidence of harm to the fetus due to amoxicillin.

Rifabutin

Reproduction studies have been carried out in rats and rabbits given rifabutin using dose levels up to 200 mg/kg (about 6 to 13 times the recommended human daily dose based on body surface area comparisons). No fetal malformations were observed in either species. In rats, given 200 mg/kg/day, (about 6 times the recommended human daily dose based on body surface area comparisons), there was a decrease in fetal viability. In rats, at 40 mg/kg/day (approximately equivalent to the recommended human daily dose based on body surface area comparisons), rifabutin caused an increase in fetal skeletal variations. In rabbits, at 80 mg/kg/day (about 5 times the recommended human daily dose based on body surface area comparisons), rifabutin caused maternal toxicity and increase in fetal skeletal anomalies.

8.2 Lactation

Risk Summary

Data from a published clinical lactation study reports that amoxicillin is present in human milk. Published adverse effects with amoxicillin exposure in the breast-fed infant include diarrhea. There are no data on the effects of amoxicillin on milk production. Limited data suggest omeprazole may be present in human milk. There are no clinical data on the effects of omeprazole on the breast-fed infant or on milk production. There are no data on the presence of rifabutin in human milk or the effects of rifabutin on the breast-fed infant or on milk production.

The developmental and health benefits of breastfeeding should be considered along with the mother’s clinical need for TALICIA and any potential adverse effects on the breast-fed child from TALICIA or from the underlying condition.

8.3 Females and Males of Reproductive Potential

Contraception

Both rifabutin and amoxicillin components of TALICIA interact with hormonal contraceptives resulting in lower levels of these contraceptives. Therefore, female patients taking hormonal contraceptives should use an additional non-hormonal highly effective method of contraception while taking TALICIA [see Drug Interactions (7.1)].

Infertility

Males

Based on findings in rodents, TALICIA may impair fertility in males of reproductive potential [see Nonclinical Toxicology (13.1)].

8.4 Pediatric Use

Safety and effectiveness of TALICIA in pediatric patients below the age of 18 years with H. pylori infection have not been established.

Esomeprazole, an enantiomer of omeprazole, was shown to decrease body weight, body weight gain, femur weight, femur length, and overall growth in juvenile rats at oral doses about 11 to 23 times a daily human dose of 120 mg esomeprazole or omeprazole based on body surface area [see Nonclinical Toxicology (13.2)].

8.5 Geriatric Use

Clinical studies of TALICIA did not include sufficient numbers of subjects aged 65 and older to determine whether they respond differently from younger subjects. Other reported clinical experience has not identified differences in responses between the elderly and younger adult patients.

Omeprazole

Omeprazole was administered to over 2000 elderly individuals (≥ 65 years of age) in clinical trials in the U.S. and Europe. There were no differences in safety and effectiveness between the elderly and younger subjects. Other reported clinical experience has not identified differences in response between the elderly and younger subjects, but greater sensitivity of some older individuals cannot be ruled out.

Amoxicillin

An analysis of clinical studies of amoxicillin was conducted to determine whether subjects aged 65 and older respond differently from younger subjects. These analyses have not identified differences in responses between the elderly and younger patients, but a greater sensitivity of some older individuals cannot be ruled out.

This drug is known to be substantially excreted by the kidney, and the risk of toxic reactions to this drug may be greater in patients with impaired renal function. Because elderly patients are more likely to have decreased renal function, it may be useful to monitor renal function in elderly patients taking TALICIA.

Rifabutin

Clinical studies of rifabutin did not include sufficient numbers of subjects aged 65 and older to determine whether they respond differently from younger subjects. Other reported clinical experience has not identified differences in responses between the elderly and younger patients.

8.6 Renal Impairment

It is recommended to avoid the use of TALICIA in patients with severe renal impairment (GFR < 30 mL/min). Amoxicillin is primarily eliminated by the kidney [see Clinical Pharmacology (12.3)].

8.7 Hepatic Impairment

It is recommended to avoid the use of TALICIA in patients with hepatic impairment. In patients with hepatic impairment (Child-Pugh Class A, B, or C) exposure to omeprazole substantially increased compared to healthy subjects [see Clinical Pharmacology (12.3)].

10 OVERDOSAGE

TALICIA

No information is available on accidental overdosage of TALICIA in humans.

In case of an overdose, patients should contact a physician, poison control center, or emergency room. The available overdosage information for each of the individual components in TALICIA (omeprazole, amoxicillin and rifabutin) are summarized below:

Omeprazole

There have been reports of overdosage with omeprazole in humans. Doses ranged up to 2400 mg (120 times the usual recommended clinical dose). Manifestations were variable, but included confusion, drowsiness, blurred vision, tachycardia, nausea, vomiting, diaphoresis, flushing, headache, dry mouth, and other adverse reactions similar to those seen in normal clinical experience [see Adverse Reactions (6.3)]. Symptoms were transient, and no serious clinical outcome has been reported when omeprazole was taken alone. No specific antidote for omeprazole overdosage is known. Omeprazole is extensively protein bound and is, therefore, not readily dialyzable. In the event of overdosage, treatment should be symptomatic and supportive.

Amoxicillin

In case of overdosage, discontinue medication, treat symptomatically, and institute supportive measures as required. A prospective study of 51 pediatric patients at a poison-control center suggested that overdosages of less than 250 mg/kg of amoxicillin are not associated with significant clinical symptoms.

Crystalluria, in some cases leading to renal failure, has also been reported after amoxicillin overdosage. In case of overdosage, adequate intake and diuresis should be maintained to reduce the risk of amoxicillin crystalluria.

Renal impairment appears to be reversible with cessation of drug administration. High blood concentrations may occur more readily in patients with impaired renal function because of decreased renal clearance of amoxicillin. Amoxicillin can be removed from circulation by hemodialysis.

Rifabutin

No information is available on accidental overdosage of rifabutin in humans.

While there is no experience in the treatment of overdose with rifabutin capsules, clinical experience with rifamycins suggests that gastric lavage to evacuate gastric contents (within a few hours of overdose), followed by instillation of an activated charcoal slurry into the stomach, may help adsorb any remaining drug from the gastrointestinal tract.

Rifabutin is 85% protein bound and distributed extensively into tissues (volume of distribution at steady state: 8 to 9 L/kg). It is not primarily excreted via the urinary route (less than 10% as unchanged drug); therefore, neither hemodialysis nor forced diuresis is expected to enhance the systemic elimination of unchanged rifabutin from the body in a patient with an overdose of rifabutin.

11 DESCRIPTION

TALICIA delayed-release capsules contain omeprazole magnesium, amoxicillin and rifabutin for oral administration. Omeprazole magnesium is included in the delayed-release component of the capsule, and amoxicillin and rifabutin are included in the immediate-release component of the capsule. Each delayed-release capsule contains:

- omeprazole 10 mg (equivalent to 10.3 mg of omeprazole magnesium)
- amoxicillin 250 mg (equivalent to 286.9 mg of amoxicillin trihydrate)
- rifabutin 12.5 mg

Omeprazole magnesium is a proton pump inhibitor. Amoxicillin and rifabutin are antibacterial drugs.

Each TALICIA delayed-release capsule contains the following inactive ingredients: crospovidone, FD&C Red 3, FD&C Yellow 6, gelatin, hydroxypropyl cellulose, hypromellose, magnesium stearate, mannitol-starch, methacrylic acid copolymer, meglumine, pregelatinized starch, silica, sodium bicarbonate, sodium lauryl sulfate, talc, titanium dioxide and triethyl citrate.

Omeprazole Magnesium

Omeprazole magnesium is a white to off-white powder with a melting point with degradation at 200 °C. The salt is slightly soluble (0.25 mg/mL) in water at 25 °C, and it is soluble in methanol. Omeprazole magnesium is 5-methoxy-2-[[(4-methoxy-3,5-dimethyl-2-pyridyl) methyl] sulfinyl]benzimidazole, (RS) magnesium salt (2:1). Omeprazole magnesium has a molecular formula of (C17H19N3O3S)2 Mg, and a molecular weight of 713.12. The structural formula is:

Amoxicillin

Amoxicillin is a semisynthetic antibacterial drug, an analog of ampicillin. Chemically it is (2S,5R,6R)-6-[(R)-(-)-2- amino-2-(p-hydroxyphenyl)acetamido]-3,3-dimethyl-7-oxo-4-thia-1-azabicyclo[3.2.0] heptane-2-carboxylic acid trihydrate. Amoxicillin has a molecular formula of C16H19N3O5S•3 H2O, and a molecular weight of 419.45. The structural formula is:

Rifabutin

Rifabutin is a red-violet powder soluble in chloroform and methanol, sparingly soluble in ethanol, and very slightly soluble in water (0.19 mg/mL). Its log P value (the base 10 logarithm of the partition coefficient between n-octanol and water) is 3.2 (n-octanol/water).

Rifabutin is (9S,12E,14S,15R,16S,17R,18R,19R,20S,21S,22E,24Z)-6-16,18,20-tetrahydroxy-1'-isobutyl-14-methoxy-7,9,15,17,19,21,25-heptamethylspiro [9,4-(epoxypentadeca[1,11,13]trienimino)-2H-furo[2',3':7,8]naphth[1,2-d] imidazole-2,4'-piperidine]-5,10,26-(3H,9H)-trione-16-acetate. Rifabutin has a molecular formula of C46H62N4O11, and a molecular weight of 847.02. The structural formula is:

12 CLINICAL PHARMACOLOGY

12.1 Mechanism of Action

TALICIA is a combination of antibacterial drugs (rifabutin, amoxicillin) and a proton pump inhibitor (omeprazole as omeprazole magnesium), an antisecretory drug [see Microbiology (12.4)].

12.2 Pharmacodynamics

After oral administration, the onset of the antisecretory effect of omeprazole occurs within one hour, with the maximum effect occurring within two hours. The antisecretory effect lasts longer than would be expected from the short (approximately one hour) plasma half-life, apparently due to prolonged binding to the parietal H+/K+ ATPase enzyme. When the drug is discontinued, secretory activity returns gradually, over 3 to 5 days. The inhibitory effect of omeprazole on acid secretion increases with repeated daily dosing.

12.3 Pharmacokinetics

The pharmacokinetic parameters of the components of TALICIA are summarized in Table 3.

Table 3: Mean (Standard Deviation) Pharmacokinetic Parameters of the Components of TALICIA

Pharmacokinetic Parametersa | Amoxicillin | Omeprazole | Rifabutin
Cmax (ng/mL) | 15,860 (3,340) | 1,281 (518) | 88 (21)
AUC24 (ng*hr/mL) | 145,788 (29,846) | 7,161 (3,533) | 1,320 (307)
Cmax =Maximum plasma concentration, AUC24 =Area under the concentration vs. 24-hour time curve
a Cmax and AUC24, estimates derived from 15 healthy subjects following administration of four TALICIA capsules three times in a day (8 hours apart) resulting in the total daily oral doses of 150 mg rifabutin, 3000 mg amoxicillin, and 120 mg omeprazole.

The absorption, distribution, and elimination related pharmacokinetic information on the components of TALICIA are provided in Table 4.

Table 4: Pharmacokinetic Properties of the Components of TALICIA

Pharmacokinetic Parameters | Amoxicillin | Omeprazole | Rifabutin
Absorption
Tmax (h), median (range)a | 2 (1.25-3) | 1.25 (0.75-1.77) | 3 (2-6)
Effect of Food:; With high-fat meala (relative to fasting) | ↓30% in Cmax; ↔ AUC∞; ↑Tmax by 1.5 hr | ↓92% in Cmax; ↓83% in AUC∞; ↑Tmax by 3 hr | ↑14% in Cmax; ↑23% in AUC∞; ↑Tmax by 2 hr
Distribution
Protein Binding | 20% | 95% | 85%
Elimination
t1/2 (h), mean (standard deviation) | 1.4 (0.2) | 1 (0.3) | 34 (25)
Metabolism
Metabolic pathways | Not significantly metabolized | - Extensively metabolized - CYP2C19 (major) responsible for the formation of hydroxyomeprazole - CYP3A4 (minor) responsible for the formation of omeprazole-sulphone - These metabolites have very little or no antisecretory activity | - Of the five metabolites that have been identified, 25-O-desacetyl and 31-hydroxy are the most predominant with a plasma metabolite: parent AUC ratio of 0.10 and 0.07, respectively - 25-O-desacetylrifabutin has an activity equal to the parent drug with up to 10% to the total antimicrobial activity
Excretion
Major route of elimination | 60% of oral dose excreted in urine in 6-8 hours (mostly as unchanged drug) | 77% of dose excreted in urine as metabolites and the remainder of the dose recovered in feces | - 53% of the oral dose was excreted in urine, primarily as metabolites - About 30% of the dose is excreted in feces - Renal and biliary clearance of unchanged drug each contribute approximately 5% to apparent oral clearance
Tmax = Time to reach Cmax, AUC∞ = Area under the concentration vs. time profile extrapolated to infinity, t1/2 = Elimination half-life, ↑ indicates increase, ↓ indicates decrease, ↔ indicates no significant change.
a Changes in Cmax, AUC∞, and Tmax estimates reported from a crossover food-effect study in 18 healthy subjects following the administration of four TALICIA capsules administered once with a high-fat, high calorie meal consisting approximately 1000 kcal (14% from protein, 53% from fat, and 33% from carbohydrates) compared to when four TALICIA capsules administered without food. Reported Tmax and t1/2 estimates are from the same study from 18 subjects (for rifabutin, from 17 subjects) who received TALICIA capsules without food.

Renal Impairment

For omeprazole, no clinically meaningful change in bioavailability was reported in patients with chronic renal impairment (CLcr between 10-62 mL/min/1.73 m^2).

Amoxicillin is primarily eliminated by the kidney [see Use in Specific Populations (8.6)].

For rifabutin, the disposition was studied following 300 mg dose in 18 patients with varying degrees of renal function. Area under plasma concentration time curve (AUC) of rifabutin increased by about 71% in patients with severe renal impairment (CLcr <30 mL/min) compared to patients with creatinine clearance (CLcr) between 61-74 mL/min. In patients with mild to moderate renal impairment (CLcr between 30-61 mL/min), the AUC of rifabutin increased by about 41%.

Hepatic Impairment

The pharmacokinetics of amoxicillin and rifabutin in patients with moderate and severe hepatic impairment are not known.

For omeprazole, in patients with chronic hepatic disease classified as Child-Pugh Class A (n=3), B (n=4), and C (n=1), the bioavailability increased to approximately 100% compared to healthy subjects, reflecting decreased first-pass effect, and the plasma half-life of the drug increased to nearly 3 hours compared with the half-life in healthy subjects of 0.5 to 1 hour. Plasma clearance averaged 70 mL/min, compared with a value of 500 to 600 mL/min in healthy subjects [see Use in Specific Populations (8.7)].

Drug Interactions

Drug interaction studies with TALICIA have not been conducted. The drug interaction information described here is based on the prescribing information of individual TALICIA components: rifabutin, omeprazole magnesium, and amoxicillin [see Drug Interactions (7)].

Effect of Omeprazole on Other Drugs

Omeprazole is a time-dependent inhibitor of CYP2C19 and can increase the systemic exposure of co-administered drugs that are CYP2C19 substrates. In addition, administration of omeprazole increases intragastric pH and can alter the systemic exposure of certain drugs that exhibit pH-dependent solubility [see Drug Interactions (7)].

Effect of Rifabutin on Other Drugs

Multiple dosing of rifabutin has been associated with induction of hepatic metabolic enzymes of the CYP3A subfamily. Rifabutin’s predominant metabolite (25-desacetyl rifabutin) may also contribute to this effect. Metabolic induction due to rifabutin is likely to produce a decrease in plasma concentrations of concomitantly administered drugs that are primarily metabolized by the CYP3A enzymes. Similarly, concomitant medications that competitively inhibit the CYP3A activity may increase plasma concentrations of rifabutin [see Drug Interactions (7)].

Drug Interactions Between TALICIA Components

CYP enzymes are involved in the metabolism of omeprazole; therefore, rifabutin mediated induction of CYP enzymes is expected to reduce systemic exposure to omeprazole.

Table 5 and Table 6 summarizes the drug interactions information from the prescribing information of omeprazole and rifabutin, respectively.

Table 5: Summary of Drug Interaction Studies with Omeprazole

Coadministered drug | Dosing regimen of coadministered drug | Dosing regimen of Omeprazole | Results
Rilpivirine | Multiple doses of 150 mg/day | Multiple doses of 20 mg/day | Rilpivirine: ↓40% AUC, ↓40% Cmax, and ↓33% Cmin
Nelfinavir | Multiple doses of 1250 mg twice daily | Multiple doses of 40 mg/day | Nelfinavir: ↓36% AUC, ↓37% Cmax, and ↓39% Cmin; M8: ↓92% in AUC, ↓89% Cmax, and ↓75% Cmin
Atazanavir | Multiple doses of 400 mg/day | Multiple doses of 40 mg/day | Atazanavir: ↓94% AUC, ↓96% Cmax, and ↓95% Cmin
Saquinavir | Saquinavir/ritonavir (1000/100 mg) twice daily for 15 days | 40 mg/day on Days 11 to 15 | Saquinavir: ↑82% AUC, ↑75% Cmax, and ↑106% Cmin
Clopidogrel | Three separate studies with 300 mg loading dose + 75 mg/day | 80 mg/day at the same time as clopidogrel in two studies and 12 hours apart in the third studies | Summary results from three studies:; - ↓41% to 46% in the exposure to the active metabolite of clopidogrel from Day 1. - Administration of clopidogrel and omeprazole at different times does not prevent interaction
Mycophenolate Mofetil (MMF) | 1000 mg dose after the last dose of omeprazole | 20 mg twice daily for four days | Mycophenolic acid (MPA)- active metabolite of MMF: ↓23% AUC and ↓52% Cmax
Cilostazol | ND | 40 mg/day for a week | Cilostazol: ↑26% AUC and ↑18% Cmax; 3,4-dihydro-cilostazol‡: ↑69% AUC and ↑29% Cmax
Diazepam | 0.1 mg/kg given intravenously | 20 mg/day concomitantly | Diazepam: ↓27% clearance and ↑36% half-life
Digoxin | ND | 20 mg/day concomitantly | Digoxin: Up to ↑30% bioavailability
Voriconazole | 400 mg twice daily for one day + 200 mg/day for 6 days | 40 mg/day for a week | Voriconazole: Four-fold ↑ in AUC and two-fold ↑in Cmax
↑ indicates increase, ↓ indicates decrease, ND=No data, AUC=Area under the concentration vs. time curve, Cmax =Maximum serum/plasma concentrations, Cmin = Minimum serum/plasma concentrations.
‡ 3,4-dihydro-cilostazol has 4-7 times the activity of cilostazol

Table 6: Summary of Drug Interaction Studies with Rifabutin

Coadministered drug | Dosing regimen of coadministered drug | Dosing regimen of Rifabutin | Study population (n) | Effect on rifabutin | Effect on coadministered drug
ANTIVIRALS
Amprenavir | 1200 mg twice daily x 10 days | 300 mg once daily x 10 days | Healthy male subjects (6) | 193%↑ AUC,; 119%↑ Cmax | ↔
Delavirdine | 400 mg TID | 300 mg once daily | HIV-infected patients (7) | 230%↑ AUC,; 128%↑ Cmax | 80%↓ AUC,; 75%↓ Cmax,; 17%↓ Cmin
Didanosine | 167 or 250 mg twice daily x 12 days | 300 or 600 mg once daily x 1 | HIV-infected patients (11) | ↔ | ↔
Fosamprenavir/; ritonavir | 700 mg twice daily plus ritonavir 100 mg twice daily x 2 weeks | 150 mg every other day x 2 weeks | Healthy subjects (15) | ↔ AUCa; 15%↓ Cmax | 35%↑ AUCb,; 36%↑ Cmax,; 36%↑ Cmin
Indinavir | 800 mg TID x 10 days | 300 mg once daily x 10 days | Healthy subjects (10) | 173%↑ AUC,; 134%↑ Cmax | 34%↓ AUC,; 25%↓ Cmax,; 39%↓ Cmin
Lopinavir/; ritonavir | 400/100 mg twice daily x 20 days | 150 mg once daily x 10 days | Healthy subjects (14) | 203%c ↑ AUC; 112%↓Cmax | ↔
Saquinavir/; ritonavir | 1000/100 mg twice daily x 14 or 22 days | 150 mg every 3 days x 21-22 days | Healthy subjects | 53%↑ AUC d,; 88% ↑ Cmax,; (n=11) | 13%↓ AUC,; 15%↓ Cmax,; (n=19)
Ritonavir | 500 mg twice daily x 10 days | 150 mg once daily x 16 days | Healthy subjects (5) | 300%↑ AUC,; 150%↑ Cmax | ND
Tipranavir/; ritonavir | 500/200 mg twice daily x 15 doses | 150 mg single dose | Healthy subjects (20) | 190%↑ AUC,; 70% ↑ Cmax | ↔
Nelfinavir | 1250 mg twice daily x 7-8 days | 150 mg once daily x 8 days | HIV-infected patients (11) | 83%↑ AUC e,; 19%↑ Cmax | ↔
Zidovudine | 100 or 200 mg q4h | 300 or 450 mg once daily | HIV-infected patients (16) | ↔ | 32%↓ AUC,; 48%↓ Cmax
ANTIFUNGALS
Fluconazole | 200 mg once daily x 2 weeks | 300 mg once daily x 2 weeks | HIV-infected patients (12) | 82%↑ AUC,; 88% ↑ Cmax | ↔
Posaconazole | 200 mg once daily x 10 days | 300 mg once daily x 17 days | Healthy subjects (8) | 72%↑ AUC,; 31%↑ Cmax | 49%↓ AUC,; 43%↓ Cmax
Itraconazole | 200 mg once daily | 300 mg once daily | HIV-Infected patients (6) | ↑f | 70%↓ AUC,; 75%↓ Cmax
Voriconazole | 400 mg twice daily x 7 days (maintenance dose) | 300 mg once daily x 7 days | Healthy male subjects (12) | 331%↑ AUC,; 195%↑ Cmax | ~100%↑ AUC,; ~100%↑ Cmax g
ANTI-PCP (Pneumocystis carinii pneumonia)
Dapsone | 50 mg once daily | 300 mg once daily | HIV-infected patients (16) | ND | 27-40%↓ AUC
Sulfamethoxazole-Trimethoprim | 800/160 mg | 300 mg once daily | HIV-infected patients (12) | ↔ | 15-20%↓ AUC
ANTI-MAC (Mycobacterium avium intracellulare complex)
Azithromycin | 500 mg once daily x 1 day, then 250 mg once daily x 9 days | 300 mg once daily | Healthy subjects (6) | ↔ | ↔
Clarithromycin | 500 mg twice daily | 300 mg once daily | HIV-infected patients (12) | 75%↑ AUC | 50%↓ AUC
ANTI-TB (Tuberculosis)
Ethambutol | 1200 mg | 300 mg once daily x 7 days | Healthy subjects (10) | ND | ↔
Isoniazid | 300 mg | 300 mg once daily x 7 days | Healthy subjects (6) | ND | ↔
OTHER
Methadone | 20-100 mg once daily | 300 mg once daily x 13 days | HIV-infected patients (24) | ND | ↔
Ethinylestradiol (EE)/; Norethindrone (NE) | 35 mg EE / 1 mg NE x 21 days | 300 mg once daily x 10 days | Healthy female subjects (22) | ND | EE:35%↓ AUC, 20%↓ Cmax,; NE: 46%↓ AUC
Theophylline | 5 mg/kg | 300 mg x 14 days | Healthy subjects (11) | ND | ↔
↑ indicates increase, ↓ indicates decrease, ↔ indicates no significant change, ND = No data, AUC=Area under the concentration vs. time curve, Cmax = Maximum serum/plasma concentrations, Cmin = Minimum serum/plasma concentrations.
a Compared to rifabutin 300 mg once daily alone
b Compared to historical control (fosamprenavir/ritonavir 700/100 mg twice daily)
c Also taking zidovudine 500 mg once daily
d Compared to rifabutin 150 mg once daily alone
e Compared to rifabutin 300 mg once daily alone
f Data from a case report
g Compared to voriconazole 200 mg twice daily alone

12.4 Microbiology

Mechanism of Action

Amoxicillin acts through the inhibition of cell wall biosynthesis that leads to the death of bacteria.

Rifabutin inhibits DNA-dependent RNA polymerase in susceptible microorganisms but not in mammalian cells.

Mechanism of Resistance

Resistance to amoxicillin is mediated primarily through beta-lactamases that cleave the beta-lactam ring of amoxicillin, rendering it inactive.

Resistance to rifabutin occurs through mutations in the DNA-dependent RNA polymerase.

Antimicrobial Activity

TALICIA therapy has been shown to be active against most clinical isolates of H. pylori. In the clinical trials, 6.4% of the pretreatment isolates had amoxicillin MIC values >0.125 mcg/mL; 17.4% had clarithromycin MIC values ≥1 mcg/mL; 43.6% had metronidazole MIC values >8 mcg/mL. All isolates had rifabutin MIC values of <1 mcg/mL. The clinical significance of these MIC values is unknown.

Susceptibility Testing

For specific information regarding susceptibility test interpretive criteria and associated test methods and quality control standards recognized by FDA for this drug, please see: https://www.fda.gov/STIC.

Effects on Gastrointestinal Microbial Ecology

Decreased gastric acidity due to any means including proton pump inhibitors, increases gastric counts of bacteria normally present in the gastrointestinal tract. Treatment with proton pump inhibitors may lead to slightly increased risk of gastrointestinal infections due to pathogens such as Salmonella and Campylobacter and, in hospitalized patients, possibly also due to Clostridioides difficile.

12.5 Pharmacogenomics

CYP2C19, a polymorphic enzyme, is involved in the metabolism of omeprazole. The CYP2C19*1 allele is fully functional while the CYP2C19*2 and *3 alleles are nonfunctional. There are other alleles associated with no or decreased CYP2C19 function. Patients carrying two fully functional alleles are normal metabolizers and those carrying two nonfunctional alleles are poor metabolizers. The systemic exposure to omeprazole varies with a patient’s metabolism status: poor metabolizers > intermediate metabolizers > normal metabolizers. Approximately 3% of Caucasians and 15 to 20% of Asians are CYP2C19 poor metabolizers.

In a pharmacokinetic study of single 20 mg omeprazole dose, the AUC of omeprazole in Asian subjects was approximately four times higher than in Caucasians. In Study 1, the safety and tolerability of TALICIA was not substantially different in CYP2C19 poor metabolizers (n = 5) and intermediate metabolizers (n = 48) compared to normal metabolizers (n = 114).

13 NONCLINICAL TOXICOLOGY

13.1 Carcinogenesis, Mutagenesis, Impairment of Fertility

No long-term studies have been performed to evaluate the effect of TALICIA on carcinogenesis, mutagenesis, or impairment of fertility.

Omeprazole

In two 24-month carcinogenicity studies in rats, omeprazole at daily doses of 1.7, 3.4, 13.8, 44.0 and 140.8 mg/kg/day (about 0.1 to 11.4 times a human dose of 120 mg/day, as expressed on a body surface area basis) produced gastric enterochromaffin-like (ECL) cell carcinoids in a dose-related manner in both males and female rats; the incidence of this effect was markedly higher in female rats, which had higher blood concentrations of omeprazole. Gastric carcinoids seldom occur in the untreated rat. In addition, ECL cell hyperplasia was present in all treated groups of both sexes. In one of these studies, female rats were treated with 13.8 mg omeprazole/kg/day (about 1 times a human dose of 120 mg/day, based on body surface area) for one year, and then followed for an additional year without the drug. No carcinoids were seen in these rats. An increased incidence of treatment-related ECL cell hyperplasia was observed at the end of one year (94% treated vs. 10% controls). By the second year the difference between treated and control rats was much smaller (46% vs. 26%) but still showed more hyperplasia in the treated group. Gastric adenocarcinoma was seen in one rat (2%). No similar tumor was seen in male or female rats treated for two years. For this strain of rat, no similar tumor has been noted historically, but a finding involving only one tumor is difficult to interpret.

In a 52-week toxicity study in Sprague-Dawley rats, brain astrocytomas were found in a small number of males that received omeprazole at dose levels of 0.4, 2, and 16 mg/kg/day (about < 0.1 to 1.3 times the human dose of 120 mg/day, based on a body surface area basis). No astrocytomas were observed in female rats in this study. In a 2-year carcinogenicity study in Sprague-Dawley rats, no astrocytomas were found in males or females at the high dose of 140.8 mg/kg/day (about 11 times the human dose of 120 mg/day on a body surface area basis). A 78-week mouse carcinogenicity study of omeprazole did not show increased tumor occurrence, but the study was not conclusive. A 26-week p53 (+/–) transgenic mouse carcinogenicity study was not positive.

Omeprazole was positive for clastogenic effects in an in vitro human lymphocyte chromosomal aberration assay, in one of two in vivo mouse micronucleus tests, and in an in vivo bone marrow cell chromosomal aberration assay. Omeprazole was negative in the in vitro Ames test, an in vitro mouse lymphoma cell forward mutation assay, and an in vivo rat liver DNA damage assay.

Omeprazole at oral doses up to 138 mg/kg/day in rats (about 11 times the human dose of 120 mg on a body surface area basis) was found to have no effect on fertility and reproductive performance.

In 24-month carcinogenicity studies in rats, a dose-related significant increase in gastric carcinoid tumors and ECL cell hyperplasia was observed in both male and female animals. Carcinoid tumors have also been observed in rats subjected to fundectomy or long-term treatment with other proton pump inhibitors or high doses of H2-receptor antagonists.

Amoxicillin

Long-term studies in animals have not been performed to evaluate carcinogenic potential. Studies to detect mutagenic potential of amoxicillin alone have not been conducted; however, the following information is available from tests on a 4:1 mixture of amoxicillin and potassium clavulanate. Amoxicillin and potassium clavulanate were non-mutagenic in the Ames bacterial mutation assay, and the yeast gene conversion assay. Amoxicillin and potassium clavulanate were weakly positive in the mouse lymphoma assay, but the trend toward increased mutation frequencies in this assay occurred at doses that were also associated with decreased cell survival. Amoxicillin and potassium clavulanate were negative in the mouse micronucleus test and in the dominant lethal assay in mice. Potassium clavulanate alone was tested in the Ames bacterial mutation assay and in the mouse micronucleus test and was negative in each of these assays. In a multi-generation reproduction study in rats, no impairment of fertility or other adverse reproductive effects were seen at doses up to 500 mg/kg (approximately 2 times the 3 g human dose based on body surface area).

Rifabutin

Long-term carcinogenicity studies were conducted with rifabutin in mice and in rats. Rifabutin was not carcinogenic in mice at doses up to 180 mg/kg/day, or approximately 36 times the recommended human daily dose. Rifabutin was not carcinogenic in the rat at doses up to 60 mg/kg/day, about 12 times the recommended human dose.

Rifabutin was not mutagenic in the bacterial mutation assay (Ames Test) using both rifabutin-susceptible and resistant strains. Rifabutin was not mutagenic in Schizosaccharomyces pombe P 1 and was not genotoxic in V-79 Chinese hamster cells, human lymphocytes in vitro, or mouse bone marrow cells in vivo.

Fertility was impaired in male rats given 160 mg/kg (32 times the recommended human daily dose).

13.2 Animal Toxicology and/or Pharmacology

A 28-day toxicity study with a 14-day recovery phase was conducted in juvenile rats with esomeprazole magnesium at doses of 70 to 280 mg/kg/day (about 6 to 23 times a daily oral human dose of 120 mg esomeprazole or omeprazole on a body surface area basis). An increase in the number of deaths at the high dose of 280 mg/kg/day was observed when juvenile rats were administered esomeprazole magnesium from postnatal day 7 through postnatal day 35. In addition, doses equal to or greater than 140 mg/kg/day (about 11 times a daily oral human dose of 120 mg esomeprazole or omeprazole on a body surface area basis), produced treatment-related decreases in body weight (approximately 14%) and body weight gain, decreases in femur weight and femur length, and affected overall growth. Comparable findings described above have also been observed in this study with another esomeprazole salt, esomeprazole strontium, at equimolar doses of esomeprazole.

14 CLINICAL STUDIES

The effectiveness and safety of TALICIA were evaluated in a randomized, double-blind, controlled study of TALICIA in treatment-naïve H. pylori-positive adult patients complaining of epigastric pain/discomfort (Study 1, NCT03198507). H. pylori infection at baseline was defined as positive by ^13C urea breath test (UBT) and follow-up upper endoscopy (culture, histology, or Campylobacter-like organism test). Patients were randomized 1:1 to TALICIA or control (total daily dose of amoxicillin 3000 mg and omeprazole 120 mg) administered for 14 consecutive days. The trial was performed in the U.S and designed to evaluate the added contribution of rifabutin to the TALICIA triple combination.

H. pylori eradication was confirmed with a negative ^13C UBT or fecal antigen test performed ≥28 days post-therapy. Patients with negative test results were considered treatment successes. Patients who tested positive for H. pylori infection were considered treatment failures, and patients with indeterminate, not assessable, or missing results from the test of cure visits underwent a repeat ^13C UBT test. Persistent indeterminate results and patients without any ^13C UBT or fecal antigen test after baseline were considered as treatment failures.

H. pylori eradication rates are shown in Table 7. The difference in response rates between TALICIA and the control was 26.1% (95% CI; 18.0, 34.1).

Table 7. Eradication Rates of H. pylori in Study 1

H. pylori Eradication | ITT Populationa
H. pylori Eradication | TALICIA N = 228 (%) | Control N =227 (%)
Success | 191 (83.8) | 131 (57.7)
Failure | 37 (16.2)b | 96 (42.3)
P-value | < 0.0001
a The Intent to Treat (ITT) population included all randomized patients who received at least one dose of study drug.
b Of those subjects classified as treatment failures, all but one subject in the TALICIA group were positive by ^13C UBT; this one subject was classified as a treatment failure due to a missing post-baseline test result.

A randomized, double-blind, placebo-controlled study of TALICIA in H. pylori-positive adult patients complaining of epigastric pain/discomfort (Study 2, NCT01980095) was performed in the U.S. and provided supportive evidence for the efficacy of TALICIA for the treatment of H. pylori infection; 77 patients taking TALICIA and 41 patients taking placebo were included in the ITT population, with an eradication rate of 76.6% (95% CI; 66.0%, 84.7%) for the TALICIA-treated patients compared to 2.4% for the placebo-treated patients. Eleven patients in the TALICIA arm and four patients in the placebo arm were classified as treatment failures due to missing ^13C UBT results at the test-of-cure visit.

16 HOW SUPPLIED/STORAGE AND HANDLING

TALICIA is supplied as an orange, opaque capsule containing omeprazole 10 mg (equivalent to omeprazole magnesium 10.3 mg), amoxicillin 250 mg and rifabutin 12.5 mg with “RHB” imprinted in black on the capsule cap and “105” imprinted in black on the capsule body. TALICIA capsules are supplied in a carton containing two bottles of 84 capsules each.

NDC 57841-1150-1 Bottle containing 84 capsules

NDC 57841-1150-2 Carton containing 2 Bottles of 84 capsules

Store at 20°C to 25°C (68°F to 77°F) [See USP Controlled Room Temperature].

Store and Dispense in original container with a child-resistant closure. Keep bottle tightly closed.

17 PATIENT COUNSELING INFORMATION

Hypersensitivity Reactions

Advise the patient to call their healthcare provided immediately if they develop new rash, skin lesions, muscle or joint pains, swelling, severe flu-like symptoms, difficulty breathing or visual symptoms [see Warnings and Precautions (5.1)].

Severe Cutaneous Adverse Reactions

Advise patients about the signs and symptoms of serious skin manifestations. Instruct patients to stop taking TALICIA immediately and promptly report the first signs or symptoms of skin rash, mucosal lesions, or any other sign of hypersensitivity [see Warnings and Precautions (5.2)].

Diarrhea

Counsel patients that diarrhea is a common problem caused by antibiotics, and it usually ends when the antibiotic is discontinued. Sometimes after starting treatment with antibiotics, patients can develop watery and bloody stools even as late as 2 or more months after having taken their last dose of the antibiotic. Patients should contact their physician as soon as possible if they experience bloody diarrhea, persistent abdominal pain, fever, or chronic diarrhea that does not resolve [see Warnings and Precautions (5.4)].

Brown-Orange Discoloration

Urine, feces, saliva, sputum, perspiration, tears, and skin may be colored brown-orange due to the rifabutin component of TALICIA and some of its metabolites. Soft contact lenses may be permanently stained. Advise patients to be treated with TALICIA of these possibilities and counsel the patient that these should resolve after therapy is completed.

Drug Interactions

Advise patients not to take St. John’s Wort, amoxicillin or other penicillin products, rifabutin or other rifamycins, over-the counter (OTC) omeprazole or other PPIs during treatment with TALICIA. Advise patients that they should not start any new medication while taking TALICIA without first speaking with their health care provider [see Warnings and Precautions (5.7)].

Contraception

Counsel females of reproductive potential who are taking oral or other forms of hormonal birth-control medications to use an additional non-hormonal highly effective method of contraception while taking TALICIA [see Warnings and Precautions (5.5)].

Embryo-Fetal Toxicity

Advise pregnant women and females of reproductive potential that TALICIA is not recommended during pregnancy because of the potential risk to a fetus. Advise females to inform their healthcare provider of a known or suspected pregnancy.

Cutaneous or Systemic Lupus

Advise patients to report any symptoms associated with cutaneous or systemic lupus erythematosus [see Warnings and Precautions (5.8)].

Acute Tubulointerstitial Nephritis

Advise the patient or caregiver to call the patient’s healthcare provider immediately if they experience signs and/or symptoms associated with acute tubulointerstitial nephritis [see Warnings and Precautions (5.6)].

Important Administration Instructions for TALICIA

- Advise patients to take four (4) TALICIA capsules three times daily (at least 4 hours apart, e.g., morning, mid-day, and evening) with food for 14 days. They should NOT crush or chew capsules.
- Advise patients to swallow TALICIA with at least 8 ounces of water.
- Advise patients not to take TALICIA with alcohol.
- Missed doses: Advise patients that if a dose is missed, and the next dose is not within 4 hours, administer as soon as possible. However, if a dose is missed and the next dose is within 4 hours, administer the missed dose as soon as possible and delay the next dose to ensure there are at least 4 hours between two doses.
  It is important for patients to complete the entire course of therapy.
- Counsel patients that antacids may be used concomitantly with TALICIA.
- Counsel patients to continue the full course of TALICIA regardless of whether or not their symptoms improve. Although change in dyspepsia symptoms may occur (either improvement or worsening), these are unlikely to be related to the H. pylori infection. Counsel patients that treatment of H. pylori infection is important due to its association with stomach ulcers, atrophic gastritis and increased risk of gastric cancer.

Antibacterial Resistance

Patients should be counseled that antibacterial drugs including TALICIA should only be used to treat bacterial infections. They do not treat viral infections (e.g., the common cold). When TALICIA is prescribed to treat a bacterial infection, patients should be told that although it is common to feel better early in the course of therapy, the medication should be taken exactly as directed. Skipping doses or not completing the full course of therapy may (1) decrease the effectiveness of the immediate treatment and (2) increase the likelihood that bacteria will develop resistance and will not be treatable by TALICIA or other antibacterial drugs in the future [see Warnings and Precautions (5.12)].

TALICIA is distributed by RedHill Biopharma Inc. Raleigh, NC

TALICIA is manufactured in Sweden for RedHill Biopharma Ltd. Tel Aviv, Israel

TALICIA is a trademark registered with the U.S. Patent and Trademark Office and used under license by RedHill Biopharma Inc.

© 2023 RedHill Biopharma Ltd. All rights reserved.

PRINCIPAL DISPLAY PANEL - Carton

NDC 57841-1150-2
Rx Only

Talicia®

(omeprazole magnesium,
amoxicillin, and rifabutin)
delayed-release capsules
10 mg*/250 mg/12.5 mg

2 BOTTLES x
84 CAPSULES

PRINCIPAL DISPLAY PANEL - Bottle Label

NDC 57841-1150-1

Talicia®
(omeprazole magnesium,
amoxicillin, and rifabutin)
delayed-release capsules
10 mg*/250 mg/12.5 mg

Rx Only

84 CAPSULES

RedHill
Biopharma